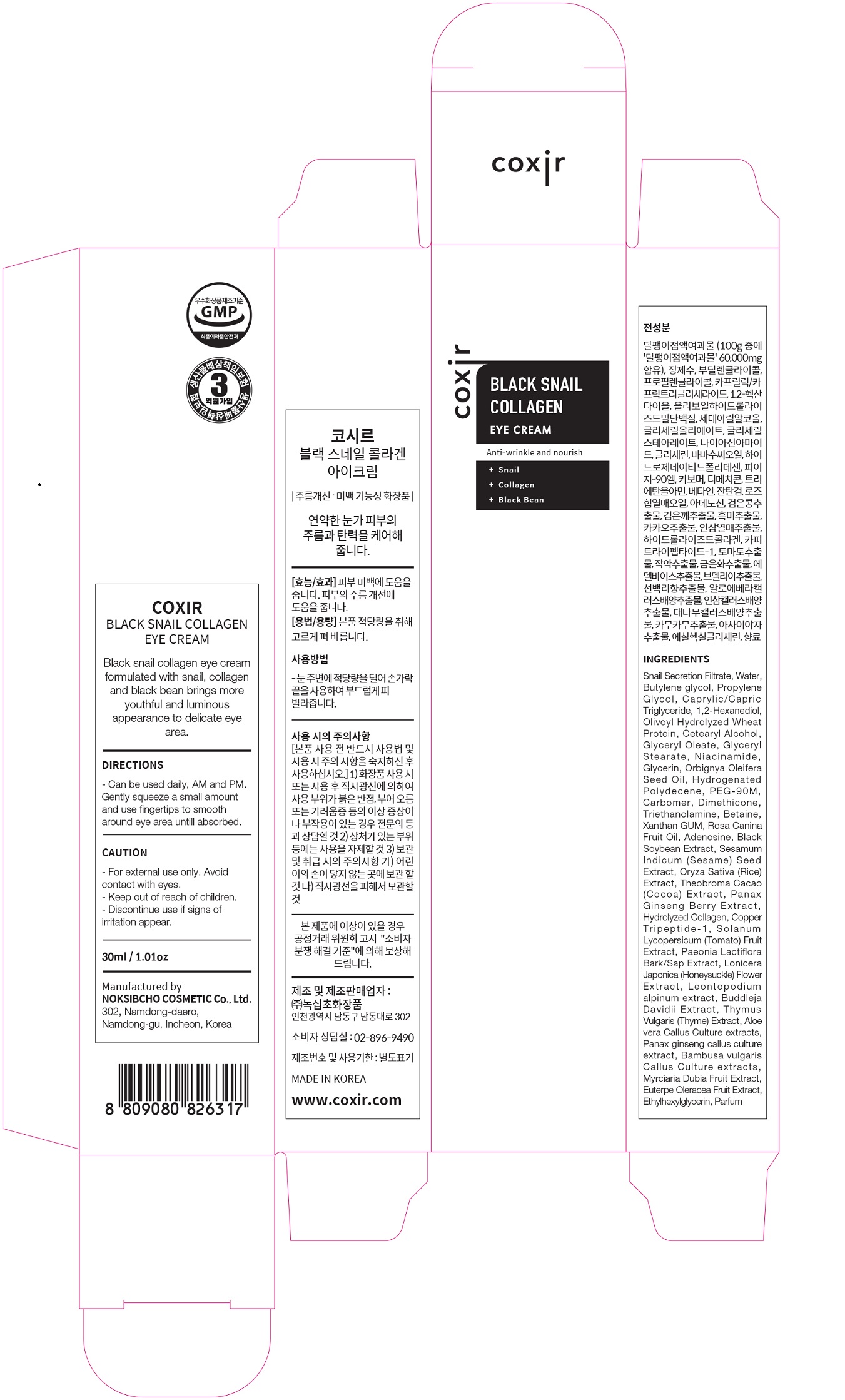 DRUG LABEL: Black Snail Collagen EyeCream
NDC: 73590-0011 | Form: CREAM
Manufacturer: NOKSIBCHO cosmetic Co., Ltd.
Category: otc | Type: HUMAN OTC DRUG LABEL
Date: 20200314

ACTIVE INGREDIENTS: SNAIL, UNSPECIFIED 60 g/100 mL
INACTIVE INGREDIENTS: WATER; BUTYLENE GLYCOL

Drug Facts

ACTIVE INGREDIENT

Snail Secretion Filtrate

INACTIVE INGREDIENT

Water
Butylene glycol
Propylene Glycol
Caprylic/Capric Triglyceride
1,2-Hexanediol
Olivoyl Hydrolyzed Wheat Protein
Cetearyl Alcohol
Glyceryl Oleate
Glyceryl Stearate
Niacinamide
Glycerin
Orbignya Oleifera Seed Oil
Hydrogenated Polydecene
PEG-90M
Carbomer
Dimethicone
Cetearyl Alcohol
Triethanolamine
Betaine
Xanthan GUM
Rosa Canina Fruit Oil
Adenosine
Black Soybean Extract
Sesamum Indicum (Sesame)
Seed Extract
Oryza Sativa (Rice) Extract
Theobroma Cacao (Cocoa) Extract
Panax Ginseng Berry Extract
Hydrolyzed Collagen
Copper Tripeptide-1
Solanum Lycopersicum (Tomato) Fruit Extract
Paeonia Lactiflora Bark/Sap Extract
Lonicera Japonica (Honeysuckle) Flower Extract
Leontopodium alpinum extract
Buddleja Davidii Extract
Water
Glycerin
Buddleja Davidii Extract
Thymus Vulgaris (Thyme) Extract
Aloe vera Callus Culture extracts
Panax ginseng callus culture extract
Bambusa vulgaris Callus Culture extracts
Myrciaria Dubia Fruit Extract
Euterpe Oleracea Fruit Extract
Ethylhexylglycerin
Parfum

PURPOSE

anti-wrinkle and nourish

keep out of reach of the children

INDICATIONS AND USAGE

apply proper amount and gently massage

WARNINGS

For external use only
When using this product

■ if the following symptoms occurs after use, stop use and consult with a skin specialist

red specks, swelling, itching

■ don’t use on the part where there is injury, eczema, or dermatitis

Keep out of reach of children

■ if swallowed, get medical help or contact a person control center immediately

DOSAGE AND ADMINISTRATION

for external use only